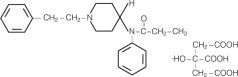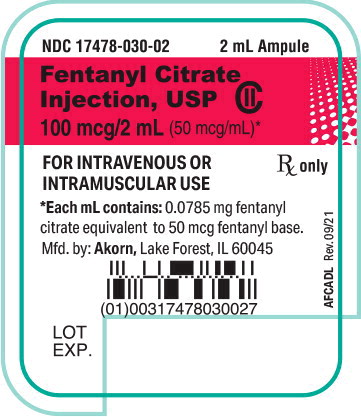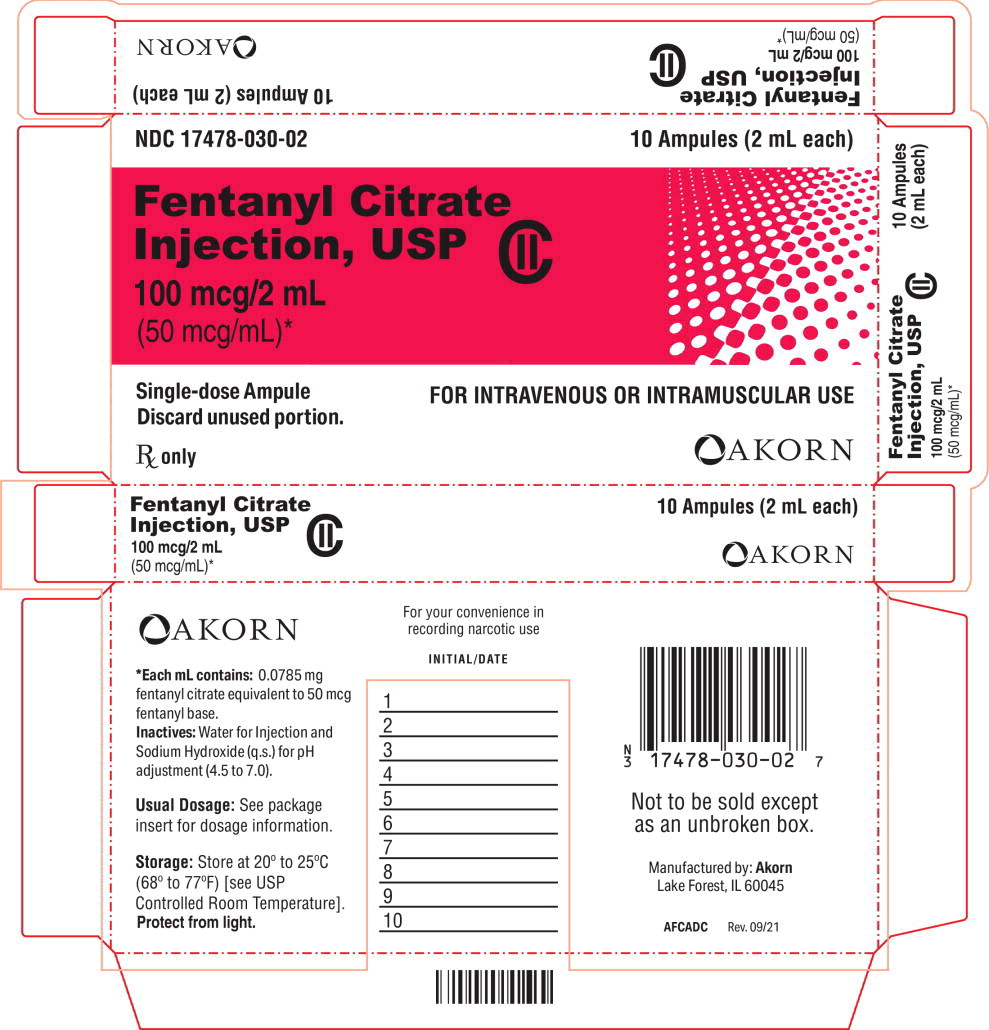 DRUG LABEL: FENTANYL CITRATE
NDC: 17478-030 | Form: INJECTION, SOLUTION
Manufacturer: Akorn
Category: prescription | Type: HUMAN PRESCRIPTION DRUG LABEL
Date: 20220909
DEA Schedule: CII

ACTIVE INGREDIENTS: FENTANYL CITRATE 50 ug/1 mL
INACTIVE INGREDIENTS: Sodium Hydroxide

HIGHLIGHTS OF PRESCRIBING INFORMATION

These highlights do not include all the information needed to use FENTANYL CITRATE INJECTION safely and effectively. See full prescribing information for FENTANYL CITRATE INJECTION.
Fentanyl Citrate Injection, for intravenous or intramuscular use, CII
Initial U.S. Approval: 1968

WARNING: RISK OF ADDICTION, ABUSE, AND MISUSE; LIFE-THREATENING RESPIRATORY DEPRESSION; CYTOCHROME P450 3A4 INTERACTION; and RISK FROM CONCOMITANT USE WITH BENZODIAZEPINES OR OTHER CNS DEPRESSANTS

WARNING: ADDICTION, ABUSE, AND MISUSE; LIFE-THREATENING RESPIRATORY DEPRESSION; CYTOCHROME P450 3A4 INTERACTION; and RISK FROM CONCOMITANT USE WITH BENZODIAZEPINES OR OTHER CNS DEPRESSANTS

See full prescribing information for complete boxed warning.

- Fentanyl Citrate Injection exposes users to risks of addiction, abuse, and misuse, which can lead to overdose and death. Assess patient's risk before prescribing and monitor regularly for these behaviors and conditions. (5.1)
- Serious, life-threatening, or fatal respiratory depression may occur. Monitor closely, especially upon initiation or following a dose increase. (5.2)
- Concomitant use with CYP3A4 inhibitors (or discontinuation of CYP3A4 inducers) can result in a fatal overdose of fentanyl. (5.3, 7, 12.3)
- Concomitant use of opioids with benzodiazepines or other central nervous system (CNS) depressants, including alcohol, may result in profound sedation, respiratory depression, coma, and death. Reserve concomitant prescribing for use in patients for whom alternative treatment options are inadequate; limit dosages and durations to the minimum required; and follow patients for signs and symptoms of respiratory depression and sedation. (5.4, 7)

1 INDICATIONS AND USAGE

Fentanyl Citrate Injection is an opioid agonist indicated for:

- analgesic action of short duration during the anesthetic periods, premedication, induction and maintenance, and in the immediate postoperative period (recovery room) as the need arises.
- use as an opioid analgesic supplement in general or regional anesthesia.
- administration with a neuroleptic as an anesthetic premedication, for the induction of anesthesia and as an adjunct in the maintenance of general and regional anesthesia.
- use as an anesthetic agent with oxygen in selected high risk patients, such as those undergoing open heart surgery or certain complicated neurological or orthopedic procedures.

2 DOSAGE AND ADMINISTRATION

- Fentanyl Citrate Injection should be administered only by persons specifically trained in the use of intravenous anesthetics and management of the respiratory effects of potent opioids.
- Ensure that an opioid antagonist, resuscitative and intubation equipment, and oxygen are readily available (2.1)
- Individualize dosing based on the factors such as age, body weight, physical status, underlying pathological condition, use of other drugs, type of anesthesia to be used, and the surgical procedure involved. (2.1)
- Initiate treatment in adults with 50 to 100 mcg (0.05 to 0.1 mg) (1 to 2 mL). (2.2)
- Initiate treatment in children 2 to 12 years of age, with a reduced dose as low as 2 to 3 mcg/kg. (2.2)

3 DOSAGE FORMS AND STRENGTHS

Solution for injection (sterile): equivalent to 50 mcg/mL fentanyl base; 2 mL, 5 mL, 10 mL and 20 mL single-dose ampules and 50 mL single-dose vial (3)

4 CONTRAINDICATIONS

- Hypersensitivity to fentanyl. (4)

5 WARNINGS AND PRECAUTIONS

- Risks of Skeletal Muscle Rigidity and Skeletal Muscle Movement: Manage with neuromuscular blocking agent. See full prescribing information for more detail on managing these risks. (5.5)
- Severe Cardiovascular Depression: Monitor during dosage initiation and titration. (5.6)
- Serotonin Syndrome: Potentially life-threatening condition could result from concomitant serotonergic drug administration. Discontinue Fentanyl Citrate Injection if serotonin syndrome is suspected. (5.7)
- Adrenal Insufficiency: If diagnosed, treat with physiologic replacement of corticosteroids, and wean patient off of the opioid. (5.8)
- Risks of Use in Patients with Increased Intracranial Pressure, Brain Tumors, or Head Injury: Monitor for sedation and respiratory depression. (5.9)

6 ADVERSE REACTIONS

Most common serious adverse reactions were respiratory depression, apnea, rigidity, and bradycardia. (6)

To report SUSPECTED ADVERSE REACTIONS, contact Akorn at 1-800-932-5676 or FDA at 1-800-FDA-1088 or www.fda.gov.medwatch.

7 DRUG INTERACTIONS

- Concomitant Use of CNS Depressants: May decrease pulmonary arterial pressure and may cause hypotension. See FPI for management instructions. For post-operative pain, start with the lowest effective dosage and monitor for potentiation of CNS depressant effects. (5.4, 7)
- Mixed Agonist/Antagonist and Partial Agonist Opioid Analgesics: Avoid use with Fentanyl Citrate Injection because they may reduce analgesic effect of Fentanyl Citrate Injection or precipitate withdrawal symptoms. (7)

8 USE IN SPECIFIC POPULATIONS

- Pregnancy: May cause fetal harm. (8.1)
- Lactation: Infants exposed to Fentanyl Citrate Injection through breast milk should be monitored for excess sedation and respiratory depression. (8.2)
- Geriatric Patients: Titrate slowly and monitor for CNS and respiratory depression. (8.5)

FULL PRESCRIBING INFORMATION

WARNING: RISK OF ADDICTION, ABUSE, AND MISUSE; LIFE-THREATENING RESPIRATORY DEPRESSION; CYTOCHROME P450 3A4 INTERACTION; and RISK FROM CONCOMITANT USE WITH BENZODIAZEPINES OR OTHER CNS DEPRESSANTS

Addiction, Abuse, and Misuse

Fentanyl Citrate Injection exposes patients and other users to the risks of opioid addiction, abuse, and misuse, which can lead to overdose and death. Assess each patient's risk prior to prescribing Fentanyl Citrate Injection, and monitor all patients regularly for the development of these behaviors and conditions [see Warnings and Precautions (5.1)].

Life-Threatening Respiratory Depression

Serious, life-threatening, or fatal respiratory depression may occur with use of Fentanyl Citrate Injection. Monitor for respiratory depression, especially during initiation of Fentanyl Citrate Injection or following a dose increase [see Warnings and Precautions (5.2)].

Cytochrome P450 3A4 Interaction

The concomitant use of Fentanyl Citrate Injection with all cytochrome P450 3A4 inhibitors may result in an increase in fentanyl plasma concentrations, which could increase or prolong adverse reactions and may cause potentially fatal respiratory depression. In addition, discontinuation of a concomitantly used cytochrome P450 3A4 inducer may result in an increase in fentanyl plasma concentration. Monitor patients receiving Fentanyl Citrate Injection and any CYP3A4 inhibitor or inducer [see Warnings and Precautions (5.3), Drug Interactions (7), Clinical Pharmacology (12.3)]

Risks From Concomitant Use With Benzodiazepines Or Other CNS Depressants

Concomitant use of opioids with benzodiazepines or other central nervous system (CNS) depressants, including alcohol, may result in profound sedation, respiratory depression, coma, and death [see Warnings and Precautions (5.4), Drug Interactions (7)].

- Reserve concomitant prescribing of Fentanyl Citrate Injection and benzodiazepines or other CNS depressants for use in patients for whom alternative treatment options are inadequate.
- Limit dosages and durations to the minimum required.
- Follow patients for signs and symptoms of respiratory depression and sedation.

1 INDICATIONS AND USAGE

Fentanyl Citrate Injection is indicated for:

- analgesic action of short duration during the anesthetic periods, premedication, induction and maintenance, and in the immediate postoperative period (recovery room) as the need arises.
- use as a narcotic analgesic supplement in general or regional anesthesia.
- administration with a neuroleptic as an anesthetic premedication, for the induction of anesthesia and as an adjunct in the maintenance of general and regional anesthesia.
- use as an anesthetic agent with oxygen in selected high risk patients, such as those undergoing open heart surgery or certain complicated neurological or orthopedic procedures.

2 DOSAGE AND ADMINISTRATION

2.1 Important Dosage and Administration Instructions

Fentanyl Citrate Injection should be administered only by persons specifically trained in the use of intravenous anesthetics and management of the respiratory effects of potent opioids.

- Ensure that an opioid antagonist, resuscitative and intubation equipment, and oxygen are readily available.
- Individualize dosage based on factors such as age, body weight, physical status, underlying pathological condition, use of other drugs, type of anesthesia to be used, and the surgical procedure involved.
- Monitor vital signs routinely.
- Discard unused portion.

As with other potent opioids, the respiratory depressant effect of fentanyl may persist longer than the measured analgesic effect. The total dose of all opioid agonists administered should be considered by the practitioner before ordering opioid analgesics during recovery from anesthesia.

If Fentanyl Citrate Injection is administered with a CNS depressant, become familiar with the properties of each drug, particularly each product's duration of action. In addition, when such a combination is used, fluids and other countermeasures to manage hypotension should be available [see Warnings and Precautions (5.4)].

Inspect parenteral drug products visually for particulate matter and discoloration prior to administration, whenever solution and container permit.

2.2 Dosage

50 mcg = 0.05 mg = 1 mL

Premedication in Adults

50 to 100 mcg (0.05 to 0.1 mg) (1 to 2 mL) may be administered intramuscularly 30 to 60 minutes prior to surgery.

Adjunct to General Anesthesia

See Dosage Range Charts below.

Table 1: Dosage Range Chart
TOTAL DOSAGE (expressed as fentanyl base)
Low Dose — 2 mcg/kg (0.002 mg/kg) (0.04 mL/kg) For use in minor, but painful, surgical procedures. May also provide some pain relief in the immediate postoperative period. | Moderate Dose — 2 to 20 mcg/kg (0.002 to 0.02 mg/kg) (0.04 to 0.4 mL/kg). For use in more major surgical procedures, in addition to adequate analgesia, may abolish some of the stress response. Expect respiratory depression requiring artificial ventilation during anesthesia and careful observation of ventilation postoperatively is essential. | High Dose — 20 to 50 mcg/kg (0.02 to 0.05 mg/kg) (0.4 to 1 mL/kg). For open heart surgery and certain more complicated neurosurgical and orthopedic procedures where surgery is more prolonged, and the stress response to surgery would be detrimental to the well-being of the patient. In conjunction with nitrous oxide/oxygen has been shown to attenuate the stress response as defined by increased levels of circulating growth hormone, catecholamine, ADH and prolactin. Expect the need for postoperative ventilation and observation due to extended postoperative respiratory depression.
MAINTENANCE DOSAGE
Low Dose — 2 mcg/kg (0.002 mg/kg) (0.04 mL/kg). Additional dosages infrequently needed in these minor procedures. | Moderate Dose — 2 to 20 mcg/kg (0.002 to 0.02 mg/kg) (0.04 to 0.4 mL/kg) - 25 to 100 mcg (0.025 to 0.1 mg) (0.5 to 2.0 mL) Administer intravenously or intramuscularly as needed when movement and/or changes in vital signs indicate surgical stress or lightening of analgesia. | High Dose — 20 to 50 mcg/kg (0.02 to 0.05 mcg/kg) (0.4 to 1.0 mL/kg). From 25 mcg (0.025 mg) (0.5 mL) to one half the initial loading dose as needed based on vital sign changes indicative of stress and lightening of analgesia. Individualize the dosage especially if the anticipated remaining operative time is short.

Adjunct to Regional Anesthesia

50 to 100 mcg (0.05 to 0.1 mg) (1 to 2 mL) may be administered intramuscularly or slowly intravenously, over one to two minutes, when additional analgesia is required.

Postoperatively (recovery room)

50 to 100 mcg (0.05 to 0.1 mg) (1 to 2 mL) may be administered intramuscularly for the control of pain, tachypnea and emergence delirium. The dose may be repeated in one to two hours as needed.

For Induction and Maintenance in Children 2 to 12 Years of Age

A reduced dose as low as 2 to 3 mcg/kg is recommended.

As a General Anesthetic

As a technique to attenuate the responses to surgical stress without the use of additional anesthetic agents, doses of 50 to 100 mcg/kg (0.05 to 0.1 mg/kg) (1 to 2 mL/kg) may be administered with oxygen and a muscle relaxant. In certain cases, doses up to 150 mcg/kg (0.15 mg/kg) (3 mL/kg) may be necessary to produce this anesthetic effect. It has been used for open heart surgery and certain other major surgical procedures in patients for whom protection of the myocardium from excess oxygen demand is particularly indicated, and for certain complicated neurological and orthopedic procedures.

3 DOSAGE FORMS AND STRENGTHS

Fentanyl Citrate Injection, USP 50 mcg/mL (equivalent to 50 mcg/mL fentanyl base) are available in: 2 mL, 5 mL, 10 mL, 20 mL single-dose ampules and 50 mL single-dose vial.

4 CONTRAINDICATIONS

Fentanyl Citrate Injection is contraindicated in patients with:

- Hypersensitivity to fentanyl (e.g., anaphylaxis) [see Adverse Reactions (6.2)]

5 WARNINGS AND PRECAUTIONS

5.1 Addiction, Abuse, and Misuse

Fentanyl Citrate Injection contains fentanyl, a Schedule II controlled substance. As an opioid, Fentanyl Citrate Injection exposes users to the risks of addiction, abuse, and misuse [see Drug Abuse and Dependence (9)].

Opioids are sought by drug abusers and people with addiction disorders and are subject to criminal diversion. Consider these risks when handling Fentanyl Citrate Injection. Strategies to reduce these risks include proper product storage and control practices for a C-II drug. Contact local state professional licensing board or state controlled substances authority for information on how to prevent and detect abuse or diversion of this product.

5.2 Life-Threatening Respiratory Depression

Serious, life-threatening, or fatal respiratory depression has been reported with the use of opioids, even when used as recommended. Respiratory depression, if not immediately recognized and treated, may lead to respiratory arrest and death. Adequate facilities should be available for postoperative monitoring and ventilation of patients administered anesthetic doses of Fentanyl Citrate Injection. It is essential that these facilities be fully equipped to handle all degrees of respiratory depression. Management of respiratory depression may include close observation, supportive measures, and use of opioid antagonists, depending on the patient's clinical status [see Overdosage (10)]. Carbon dioxide (CO2) retention from opioid-induced respiratory depression can exacerbate the sedating effects of opioids.

To reduce the risk of respiratory depression, proper dosing and titration of Fentanyl Citrate Injection are essential. As with other potent opioids, the respiratory depressant effect of Fentanyl Citrate Injection may persist longer than the measured analgesic effect. The total dose of all opioid agonists administered should be considered by the practitioner before ordering opioid analgesics during recovery from anesthesia.

Certain forms of conduction anesthesia, such as spinal anesthesia and some peridural anesthetics, can alter respiration by blocking intercostal nerves through other mechanisms [see Clinical Pharmacology (12.2)]. Fentanyl Citrate Injection can also alter respiration. Therefore, when Fentanyl Citrate Injection is used to supplement these forms of anesthesia, the anesthetist should be familiar with the physiological alterations involved, and be prepared to manage them in the patients selected for these forms of anesthesia.

Patients with significant chronic obstructive pulmonary disease or cor pulmonale, and those with a substantially decreased respiratory reserve, hypoxia, hypercapnia, or pre-existing respiratory depression are at increased risk of decreased respiratory drive including apnea, even at recommended dosages of Fentanyl Citrate Injection. Elderly, cachectic, or debilitated patients may have altered pharmacokinetics or altered clearance compared to younger, healthier patients resulting in greater risk for respiratory depression.

Monitor such patients closely including vital signs, particularly when initiating and titrating Fentanyl Citrate Injection and when Fentanyl Citrate Injection is given concomitantly with other drugs that depress respiration. To reduce the risk of respiratory depression, proper dosing and titration of Fentanyl Citrate Injection are essential [see Dosage and Administration (2.1)].

Opioids can cause sleep-related breathing disorders including central sleep apnea (CSA) and sleep-related hypoxemia. Opioid use increases the risk of CSA in a dose-dependent fashion. In patients who present with CSA, consider decreasing the opioid dosage using best practices for opioid taper [see Dosage and Administration (2.1)].

5.3 Risks of Concomitant Use or Discontinuation of Cytochrome P450 3A4 Inhibitors and Inducers

Concomitant use of Fentanyl Citrate Injection with a CYP3A4 inhibitor, such as macrolide antibiotics (e.g., erythromycin), azole-antifungal agents (e.g., ketoconazole), and protease inhibitors (e.g., ritonavir), may increase plasma concentrations of fentanyl and prolong opioid adverse reactions, which may exacerbate respiratory depression [see Warnings and Precautions (5.2)], particularly when an inhibitor is added after a stable dose of Fentanyl Citrate Injection is achieved. Similarly, discontinuation of a CYP3A4 inducer, such as rifampin, carbamazepine, and phenytoin, in Fentanyl Citrate Injection-treated patients may increase fentanyl plasma concentrations and prolong opioid adverse reactions. When using Fentanyl Citrate Injection with CYP3A4 inhibitors or discontinuing CYP3A4 inducers in Fentanyl Citrate Injection-treated patients, monitor patients closely at frequent intervals and consider dosage reduction of Fentanyl Citrate Injection [see Dosage and Administration (2.1), Drug Interactions (7)].

Concomitant use of Fentanyl Citrate Injection with CYP3A4 inducers or discontinuation of an CYP3A4 inhibitor could result in lower than expected fentanyl plasma concentrations and, decrease efficacy. When using Fentanyl Citrate Injection with CYP3A4 inducers or discontinuing CYP3A4 inhibitors, monitor patients closely at frequent intervals and consider increasing the Fentanyl Citrate Injection dosage [see Dosage and Administration (2.1), Drug Interactions (7)].

5.4 Risks from Concomitant Use with Benzodiazepines or Other CNS Depressants

When benzodiazepines or other CNS depressants are used with Fentanyl Citrate Injection, pulmonary arterial pressure may be decreased. This fact should be considered by those who conduct diagnostic and surgical procedures where interpretation of pulmonary arterial pressure measurements might determine final management of the patient. When high dose or anesthetic dosages of Fentanyl Citrate Injection are employed, even relatively small dosages of diazepam may cause cardiovascular depression.

When Fentanyl Citrate Injection is used with CNS depressants, hypotension can occur. If it occurs, consider the possibility of hypovolemia and manage with appropriate parenteral fluid therapy. When operative conditions permit, consider repositioning the patient to improve venous return to the heart. Exercise care in moving and repositioning of patients because of the possibility of orthostatic hypotension. If volume expansion with fluids plus other countermeasures do not correct hypotension, consider administration of pressor agents other than epinephrine. Epinephrine may paradoxically decrease blood pressure in patients treated with a neuroleptic that blocks alpha adrenergic activity.

Profound sedation, respiratory depression, coma, and death may result from the concomitant use of Fentanyl Citrate Injection with benzodiazepines or other CNS depressants (e.g., nonbenzodiazepine sedatives/hypnotics, anxiolytics, tranquilizers, muscle relaxants, general anesthetics, antipsychotics, other opioids, alcohol).

If the decision is made to manage postoperative pain with Fentanyl Citrate Injection concomitantly with a benzodiazepine or other CNS depressant, start dosing with the lowest effective dosage and titrate based on clinical response. Follow patients closely for signs and symptoms of respiratory depression, sedation, and hypotension. Fluids or other measures to counter hypotension should be available [see Drug Interactions (7)].

5.5 Risks of Muscle Rigidity and Skeletal Muscle Movement

Fentanyl Citrate Injection may cause muscle rigidity, particularly involving the muscles of respiration. The incidence and severity of muscle rigidity is dose related. These effects are related to the dose and speed of injection. Skeletal muscle rigidity also has been reported to occur or recur infrequently in the extended postoperative period usually following high dose administration. In addition, skeletal muscle movements of various groups in the extremities, neck, and external eye have been reported during induction of anesthesia with Fentanyl Citrate Injection; these reported movements have, on rare occasions, been strong enough to pose patient management problems.

These effects are related to the dose and speed of injection and its incidence can be reduced by: 1) administration of up to 1/4 of the full paralyzing dose of a non-depolarizing neuromuscular blocking agent just prior to administration of Fentanyl Citrate Injection; 2) administration of a full paralyzing dose of a neuromuscular blocking agent following loss of eyelash reflex when Fentanyl Citrate Injection is used in anesthetic doses titrated by slow intravenous infusion; or, 3) simultaneous administration of Fentanyl Citrate Injection and a full paralyzing dose of a neuromuscular blocking agent when Fentanyl Citrate Injection is used in rapidly administered anesthetic dosages. The neuromuscular blocking agent used should be compatible with the patient's cardiovascular status.

5.6 Severe Cardiovascular Depression

Fentanyl Citrate Injection may cause severe bradycardia, severe hypotension including orthostatic hypotension, and syncope. There is increased risk in patients whose ability to maintain blood pressure has already been compromised by a reduced blood volume or concurrent administration of certain CNS depressant drugs (e.g., phenothiazines or general anesthetics) [see Drug Interactions (7)]. In patients with circulatory shock, Fentanyl Citrate Injection may cause vasodilation that can further reduce cardiac output and blood pressure. Monitor these patients for signs of hypotension after initiating or titrating the dosage of Fentanyl Citrate Injection.

5.7 Serotonin Syndrome with Concomitant Use of Serotonergic Drugs

Cases of serotonin syndrome, a potentially life-threatening condition, have been reported during concomitant use of fentanyl with serotonergic drugs. Serotonergic drugs include selective serotonin reuptake inhibitors (SSRIs), serotonin and norepinephrine reuptake inhibitors (SNRIs), tricyclic antidepressants (TCAs), triptans, 5-HT3 receptor antagonists, drugs that affect the serotonergic neurotransmitter system (e.g., mirtazapine, trazodone, tramadol), certain muscle relaxants (i.e., cyclobenzaprine, metaxalone), and drugs that impair metabolism of serotonin (including MAO inhibitors, both those intended to treat psychiatric disorders and also others, such as linezolid and intravenous methylene blue) [see Drug Interactions (7)]. This may occur within the recommended dosage range.

Serotonin syndrome symptoms may include mental status changes (e.g., agitation, hallucinations, coma), autonomic instability (e.g., tachycardia, labile blood pressure, hyperthermia), neuromuscular aberrations (e.g., hyperreflexia, incoordination, rigidity), and/or gastrointestinal symptoms (e.g., nausea, vomiting, diarrhea). The onset of symptoms generally occurs within several hours to a few days of concomitant use, but may occur later than that. Discontinue Fentanyl Citrate Injection if serotonin syndrome is suspected.

5.8 Adrenal Insufficiency

Cases of adrenal insufficiency have been reported with opioid use, more often following greater than one month of use. Presentation of adrenal insufficiency may include non-specific symptoms and signs including nausea, vomiting, anorexia, fatigue, weakness, dizziness, and low blood pressure. If adrenal insufficiency is suspected, confirm the diagnosis with diagnostic testing as soon as possible. If adrenal insufficiency is diagnosed, treat with physiologic replacement doses of corticosteroids. Wean the patient off of the opioid to allow adrenal function to recover and continue corticosteroid treatment until adrenal function recovers. Other opioids may be tried as some cases reported use of a different opioid without recurrence of adrenal insufficiency. The information available does not identify any particular opioids as being more likely to be associated with adrenal insufficiency.

5.9 Risks of Use in Patients with Increased Intracranial Pressure, Brain Tumors, or Head Injury

In patients who may be susceptible to the intracranial effects of CO2 retention (e.g., those with evidence of increased intracranial pressure or brain tumors), Fentanyl Citrate Injection may reduce respiratory drive, and the resultant CO2 retention can further increase intracranial pressure. Monitor such patients for signs of increasing intracranial pressure.

5.10 Risks of Use in Patients with Gastrointestinal Conditions

Fentanyl may cause spasm of the sphincter of Oddi. Opioids may cause increases in serum amylase. Monitor patients with biliary tract disease, including acute pancreatitis for worsening symptoms.

5.11 Increased Risk of Seizures in Patients with Seizure Disorders

Fentanyl may increase the frequency of seizures in patients with seizure disorders, and may increase the risk of seizures occurring in other clinical settings associated with seizures. Monitor patients with a history of seizure disorders for worsened seizure control during Fentanyl Citrate Injection therapy.

5.12 Risks of Driving and Operating Machinery

Fentanyl Citrate Injection may impair the mental or physical abilities needed to perform potentially hazardous activities such as driving a car or operating machinery. Warn patients not to drive or operate dangerous machinery after Fentanyl Citrate Injection administration.

5.13 Risks due to Interaction with Neuroleptic Agents

Many neuroleptic agents have been associated with QT prolongation, torsades de pointes, and cardiac arrest. Administer neuroleptic agents with extreme caution in the presence of risk factors for development of prolonged QT syndrome and torsades de pointes, such as: 1) clinically significant bradycardia (less than 50 bpm), 2) any clinically significant cardiac disease, including baseline prolonged QT interval, 3) treatment with Class I and Class III antiarrhythmics, 4) treatment with monoamine oxidase inhibitors (MAOI's), 5) concomitant treatment with other drug products known to prolong the QT interval and 6) electrolyte imbalance, in particular hypokalemia and hypomagnesemia, or concomitant treatment with drugs (e.g. diuretics) that may cause electrolyte imbalance.

Elevated blood pressure, with and without pre-existing hypertension, has been reported following administration of Fentanyl Citrate Injection combined with a neuroleptic. This might be due to unexplained alterations in sympathetic activity following large doses; however, it is also frequently attributed to anesthetic and surgical stimulation during light anesthesia.

ECG monitoring is indicated when a neuroleptic agent is used in conjunction with Fentanyl Citrate Injection as an anesthetic premedication, for the induction of anesthesia, or as an adjunct in the maintenance of general or regional anesthesia.

When Fentanyl Citrate Injection is used with a neuroleptic and an EEG is used for postoperative monitoring, the EEG pattern may return to normal slowly.

6 ADVERSE REACTIONS

The following serious adverse reactions are described, or described in greater detail, in other sections:

- Addiction, Abuse, and Misuse [see Warnings and Precautions (5.1)]
- Life-Threatening Respiratory Depression [see Warnings and Precautions (5.2)]
- Interactions with Benzodiazepines or Other CNS Depressants [see Warnings and Precautions (5.4)
- Severe Cardiovascular Depression [see Warnings and Precautions (5.6)]
- Serotonin Syndrome [see Warnings and Precautions (5.7)]
- Gastrointestinal Adverse Reactions [see Warnings and Precautions (5.10)]
- Seizures [see Warnings and Precautions (5.11)]

The following adverse reactions associated with the use of fentanyl were identified in clinical studies or postmarketing reports. Because some of these reactions were reported voluntarily from a population of uncertain size, it is not always possible to reliably estimate their frequency or establish a causal relationship to drug exposure.

As with opioid agonists, the most common serious adverse reactions reported to occur with fentanyl are respiratory depression, apnea, rigidity, and bradycardia; if these remain untreated, respiratory arrest, circulatory depression or cardiac arrest could occur. Other adverse reactions that have been reported are hypertension, hypotension, dizziness, blurred vision, nausea, emesis, diaphoresis, pruritus, urticaria, laryngospasm and anaphylaxis.

It has been reported that secondary rebound respiratory depression may occasionally occur postoperatively.

When a tranquilizer is used with Fentanyl Citrate Injection, the following adverse reactions can occur: chills and/or shivering, restlessness, and postoperative hallucinatory episodes (sometimes associated with transient periods of mental depression); extrapyramidal symptoms (dystonia, akathisia, and oculogyric crisis) have been observed up to 24 hours postoperatively. When they occur, extrapyramidal symptoms can usually be controlled with anti-parkinson agents. Postoperative drowsiness is also frequently reported following the use of neuroleptics with fentanyl citrate.

Cases of cardiac dysrhythmias, cardiac arrest, and death have been reported following the use of fentanyl citrate with a neuroleptic agent.

Serotonin syndrome: Cases of serotonin syndrome, a potentially life-threatening condition, have been reported during concomitant use of opioids with serotonergic drugs.

Adrenal insufficiency: Cases of adrenal insufficiency have been reported with opioid use, more often following greater than one month of use.

Anaphylaxis: Anaphylaxis has been reported with ingredients contained in Fentanyl Citrate Injection.

Androgen deficiency: Cases of androgen deficiency have occurred with chronic use of opioids [see Clinical Pharmacology (12.2)].

7 DRUG INTERACTIONS

Table 2 includes clinically significant drug interactions with Fentanyl Citrate Injection.

Table 2: Clinically Significant Drug Interactions with Fentanyl Citrate Injection
Inhibitors of CYP3A4
Clinical Impact: | The concomitant use of Fentanyl Citrate Injection and CYP3A4 inhibitors can increase the plasma concentration of fentanyl, resulting in increased or prolonged opioid effects, particularly when an inhibitor is added after a stable dose of Fentanyl Citrate Injection is achieved [see Warnings and Precautions (5.3)]. After stopping a CYP3A4 inhibitor, as the effects of the inhibitor decline, the fentanyl plasma concentration will decrease [see Clinical Pharmacology (12.3)], resulting in decreased opioid efficacy or a withdrawal syndrome in patients who had developed physical dependence to fentanyl.
Intervention: | If concomitant use is necessary, consider dosage reduction of Fentanyl Citrate Injection until stable drug effects are achieved. Monitor patients for respiratory depression and sedation at frequent intervals. If a CYP3A4 inhibitor is discontinued, consider increasing the Fentanyl Citrate Injection dosage until stable drug effects are achieved. Monitor for signs of opioid withdrawal.
Examples: | Macrolide antibiotics (e.g., erythromycin), azole-antifungal agents (e.g. ketoconazole), protease inhibitors (e.g., ritonavir), grapefruit juice
CYP3A4 Inducers
Clinical Impact: | The concomitant use of Fentanyl Citrate Injection and CYP3A4 inducers can decrease the plasma concentration of fentanyl [see Clinical Pharmacology (12.3)], resulting in decreased efficacy or onset of a withdrawal syndrome in patients who have developed physical dependence to fentanyl [see Warnings and Precautions (5.3)]. After stopping a CYP3A4 inducer, as the effects of the inducer decline, the fentanyl plasma concentration will increase [see Clinical Pharmacology (12.3)], which could increase or prolong both the therapeutic effects and adverse reactions, and may cause serious respiratory depression.
Intervention: | If concomitant use is necessary, consider increasing the Fentanyl Citrate Injection dosage until stable drug effects are achieved. Monitor for signs of opioid withdrawal. If a CYP3A4 inducer is discontinued, consider Fentanyl Citrate Injection dosage reduction and monitor for signs of respiratory depression.
Examples: | Rifampin, carbamazepine, phenytoin
Benzodiazepines and Other Central Nervous System (CNS) Depressants
Clinical Impact: | The concomitant use of Fentanyl Citrate Injection with CNS depressants may result in decreased pulmonary artery pressure and may cause hypotension. Even small dosages of diazepam may cause cardiovascular depression when added to high dose or anesthetic dosages of Fentanyl Citrate Injection. As postoperative analgesia, concomitant use of Fentanyl Citrate Injection can increase the risk of hypotension, respiratory depression, profound sedation, coma, and death.
Intervention: | As postoperative analgesia, start with a lower dose of Fentanyl Citrate Injection and monitor patients for signs of respiratory depression, sedation, and hypotension. Fluids or other measures to counter hypotension should be available. [see Warnings and Precautions (5.4)].
Examples: | Benzodiazepines and other sedatives/hypnotics, anxiolytics, tranquilizers, muscle relaxants, general anesthetics, antipsychotics, other opioids, alcohol.
Serotonergic Drugs
Clinical Impact: | The concomitant use of opioids with other drugs that affect the serotonergic neurotransmitter system has resulted in serotonin syndrome [see Warnings and Precautions 5.7].
Intervention: | If concomitant use is warranted, carefully observe the patient, particularly during treatment initiation and dose adjustment. Discontinue Fentanyl Citrate Injection if serotonin syndrome is suspected.
Examples: | Selective serotonin reuptake inhibitors (SSRIs), serotonin and norepinephrine reuptake inhibitors (SNRIs), tricyclic antidepressants (TCAs), triptans, 5-HT3 receptor antagonists, drugs that effect the serotonin neurotransmitter system (e.g., mirtazapine, trazodone, tramadol), certain muscle relaxants (i.e., cyclobenzaprine, metaxalone), monoamine oxidase (MAO) inhibitors (those intended to treat psychiatric disorders and also others, such as linezolid and intravenous methylene blue).
Monoamine Oxidase Inhibitors
Clinical Impact: | MAOI interactions with opioids may manifest as serotonin syndrome or opioid toxicity (e.g., respiratory depression, coma) [see Warnings and Precautions (5.2)]
Intervention: | The use of Fentanyl Citrate Injection is not recommended for patients taking MAOIs or within 14 days of stopping such treatment.
Examples: | phenelzine, tranylcypromine, linezolid
Mixed Agonist/Antagonist and Partial Agonist Opioid Analgesics
Clinical Impact: | May reduce the analgesic effect of Fentanyl Citrate Injection and/or precipitate withdrawal symptoms.
Intervention: | Avoid concomitant use.
Examples: | butorphanol, nalbuphine, pentazocine, buprenorphine
Muscle Relaxants
Clinical Impact: | Fentanyl may enhance the neuromuscular blocking action of skeletal muscle relaxants and produce an increased degree of respiratory depression.
Intervention: | Monitor patients for signs of respiratory depression that may be greater than otherwise expected and decrease the dosage of Fentanyl Citrate Injection and/or the muscle relaxant as necessary.
Diuretics
Clinical Impact: | Opioids can reduce the efficacy of diuretics by inducing the release of antidiuretic hormone.
Intervention: | Monitor patients for signs of diminished diuresis and/or effects on blood pressure and increase the dosage of the diuretic as needed.
Anticholinergic Drugs
Clinical Impact: | The concomitant use of anticholinergic drugs may increase risk of urinary retention and/or severe constipation, which may lead to paralytic ileus.
Intervention: | Monitor patients for signs of urinary retention or reduced gastric motility when Fentanyl Citrate Injection is used concomitantly with anticholinergic drugs.
Neuroleptics
Clinical Impact: | Elevated blood pressure, with and without pre-existing hypertension, has been reported following administration of fentanyl combined with a neuroleptic [see Warnings and Precautions (5.13)].
Intervention: | ECG monitoring is indicated when a neuroleptic agent is used in conjunction with Fentanyl Citrate Injection as an anesthetic premedication, for the induction of anesthesia, or as an adjunct in the maintenance of general or regional anesthesia.
Nitrous oxide
Clinical Impact: | Nitrous oxide has been reported to produce cardiovascular depression when given with higher doses of Fentanyl Citrate Injection.
Intervention: | Monitor patients for signs of cardiovascular depression that may be greater than otherwise expected.

8 USE IN SPECIFIC POPULATIONS

8.1 Pregnancy

Risk Summary

Prolonged use of opioid analgesics during pregnancy may cause neonatal opioid withdrawal syndrome. Available data with Fentanyl Citrate Injection in pregnant women are insufficient to inform a drug-associated risk for major birth defects and miscarriage.

In animal reproduction studies, fentanyl administration to pregnant rats during organogenesis was embryocidal at doses within the range of the human recommended dosing. No evidence of malformations was noted in animal studies completed to date [see Data].

The estimated background risk of major birth defects and miscarriage for the indicated population is unknown. All pregnancies have a background risk of birth defect, loss, or other adverse outcomes. In the U.S. general population, the estimated background risk of major birth defects and miscarriage in clinically recognized pregnancies is 2% to 4% and 15% to 20%, respectively.

Clinical Considerations

Fetal/Neonatal Adverse Reactions

Prolonged use of opioid analgesics during pregnancy for medical or nonmedical purposes can result in physical dependence in the neonate and neonatal opioid withdrawal syndrome shortly after birth.

Neonatal opioid withdrawal syndrome presents as irritability, hyperactivity and abnormal sleep pattern, high pitched cry, tremor, vomiting, diarrhea, and failure to gain weight. The onset, duration, and severity of neonatal opioid withdrawal syndrome vary based on the specific opioid used, duration of use, timing and amount of last maternal use, and rate of elimination of the drug by the newborn. Observe newborns for symptoms of neonatal opioid withdrawal syndrome and manage accordingly.

Labor or Delivery

Opioids cross the placenta and may produce respiratory depression and psycho-physiologic effects in neonates. An opioid antagonist, such as naloxone, must be available for reversal of opioid-induced respiratory depression in the neonate. Fentanyl Citrate Injection is not recommended for use in pregnant women during or immediately prior to labor, when other analgesic techniques are more appropriate. Opioid analgesics, including Fentanyl Citrate Injection, can prolong labor through actions which temporarily reduce the strength, duration, and frequency of uterine contractions. However, this effect is not consistent and may be offset by an increased rate of cervical dilation, which tends to shorten labor. Monitor neonates exposed to opioid analgesics during labor for signs of excess sedation and respiratory depression.

Data

Animal Data

Fentanyl has been shown to embryocidal in pregnant rats at doses of 30 mcg/kg intravenously (0.05 times the human dose of 100 mcg/kg on a mg/m^2 basis) and 160 mcg/kg subcutaneously (0.26 times the human dose of 100 mcg/kg on a mg/m^2 basis). There was no evidence of teratogenicity reported.

No evidence of malformations or adverse effects on the fetus was reported in a published study in which pregnant rats were administered fentanyl continuously via subcutaneously implanted osmotic minipumps at doses of 10, 100, or 500 mcg/kg/day starting 2-weeks prior to breeding and throughout pregnancy. The high dose was approximately 0.81 times the human dose of 100 mcg/kg on a mg/m^2 basis.

8.2 Lactation

Risk Summary

Fentanyl is present in breast milk. One published lactation study reports a relative infant dose of fentanyl of 0.38%. However, there is insufficient information to determine the effects of fentanyl on the breastfed infant and the effects of fentanyl on milk production.

The developmental and health benefits of breastfeeding should be considered along with the mother's clinical need for Fentanyl Citrate Injection and any potential adverse effects on the breastfed infant from Fentanyl Citrate Injection or from the underlying maternal condition.

Clinical Considerations

Monitor infants exposed to fentanyl through breast milk for excess sedation and respiratory depression. Withdrawal symptoms can occur in breastfed infants when maternal administration of an opioid analgesic is stopped, or when breast-feeding is stopped.

8.3 Females and Males of Reproductive Potential

Infertility

Chronic use of opioids may cause reduced fertility in females and males of reproductive potential. It is not known whether these effects on fertility are reversible [see Adverse Reactions (6.2), Clinical Pharmacology (12.2), Nonclinical Toxicology (13.1)].

8.4 Pediatric Use

The safety and efficacy of Fentanyl Citrate Injection in children under two years of age have not been established.

Rare cases of unexplained clinically significant methemoglobinemia have been reported in premature neonates undergoing emergency anesthesia and surgery which included the combined use of fentanyl, pancuronium, and atropine. A direct cause and effect relationship between the combined use of these drugs and the reported cases of methemoglobinemia has not been established.

8.5 Geriatric Use

Elderly patients (aged 65 years or older) may have increased sensitivity to fentanyl. In general, use caution when selecting a dosage for an elderly patient, usually starting at the low end of the dosing range, reflecting the greater frequency of decreased hepatic, renal, or cardiac function and of concomitant disease or other drug therapy.

Respiratory depression is the chief risk for elderly patients treated with opioids, and has occurred after large initial doses were administered to patients who were not opioid-tolerant or when opioids were co-administered with other agents that depress respiration. Titrate the dosage of Fentanyl Citrate Injection slowly in geriatric patients and monitor closely for signs of central nervous system and respiratory depression [see Warnings and Precautions (5.2)].

Fentanyl is known to be substantially excreted by the kidney, and the risk of adverse reactions to this drug may be greater in patients with impaired renal function. Because elderly patients are more likely to have decreased renal function, care should be taken in dose selection, and it may be useful to monitor renal function.

8.6 Hepatic Impairment

Fentanyl Citrate Injection should be administered with caution to patients with liver dysfunction because of the extensive hepatic metabolism. Reduce the dosage as needed and monitor closely for signs of respiratory depression, sedation, and hypotension.

8.7 Renal Impairment

Fentanyl Citrate Injection should be administered with caution to patients with kidney dysfunction because of the renal excretion of fentanyl citrate and its metabolites. Reduce the dosage as needed and monitor for signs of respiratory depression, sedation, and hypotension.

9 DRUG ABUSE AND DEPENDENCE

9.1 Controlled Substance

Fentanyl Citrate Injection contains fentanyl, a Schedule II controlled substance.

9.2 Abuse

Fentanyl Citrate Injection contains fentanyl, a substance with a high potential for abuse similar to other opioids including hydrocodone, hydromorphone, methadone, morphine, oxycodone, oxymorphone, and tapentadol. Fentanyl Citrate Injection can be abused and is subject to misuse, addiction, and criminal diversion [see Warnings and Precautions (5.1)].

Drug addiction is a cluster of behavioral, cognitive, and physiological phenomena that develop after repeated substance use and includes:

a strong desire to take the drug, difficulties in controlling its use, persisting in its use despite harmful consequences, a higher priority given to drug use than to other activities and obligations, increased tolerance, and sometimes a physical withdrawal.

Fentanyl Citrate Injection, like other opioids, can be diverted for non-medical use into illicit channels of distribution. Careful recordkeeping of prescribing information, including quantity, frequency, and renewal requests, as required by state and federal law, is strongly advised.

Risks Specific to Abuse of Fentanyl Citrate Injection

Abuse of Fentanyl Citrate Injection poses a risk of overdose and death. The risk is increased with concurrent use of Fentanyl Citrate Injection with alcohol and other central nervous system depressants.

Parenteral drug abuse is commonly associated with transmission of infectious diseases such as hepatitis and HIV.

9.3 Dependence

Both tolerance and physical dependence can develop during chronic opioid therapy. Tolerance is the need for increasing doses of opioids to maintain a defined effect such as analgesia (in the absence of disease progression or other external factors). Tolerance may occur to both the desired and undesired effects of drugs, and may develop at different rates for different effects.

Physical dependence results in withdrawal symptoms after abrupt discontinuation or a significant dosage reduction of a drug. Withdrawal also may be precipitated through the administration of drugs with opioid antagonist activity (e.g., naloxone, nalmefene), mixed agonist/ antagonist analgesics (e.g., pentazocine, butorphanol, nalbuphine), or partial agonists (e.g., buprenorphine). Physical dependence may not occur to a clinically significant degree until after several days to weeks of continued opioid usage.

10 OVERDOSAGE

Clinical Presentation

Acute overdose with Fentanyl Citrate Injection can be manifested by respiratory depression, somnolence progressing to stupor or coma, skeletal muscle flaccidity, cold and clammy skin, constricted pupils, and, in some cases, pulmonary edema, bradycardia, hypotension, partial or complete airway obstruction, atypical snoring, and death. Marked mydriasis rather than miosis may be seen with hypoxia in overdose situations [see Clinical Pharmacology (12.2)].

Treatment of Overdose

In case of overdose, priorities are the reestablishment of a patent and protected airway and institution of assisted or controlled ventilation, if needed. Employ other supportive measures (including oxygen and vasopressors) in the management of circulatory shock and pulmonary edema as indicated. Cardiac arrest or arrhythmias will require advanced life-support techniques.

The opioid antagonists, naloxone or nalmefene, are specific antidotes to respiratory depression resulting from opioid overdose. For clinically significant respiratory or circulatory depression secondary to fentanyl overdose, administer an opioid antagonist. Opioid antagonists should not be administered in the absence of clinically significant respiratory or circulatory depression secondary to fentanyl overdose.

Because the duration of opioid reversal is expected to be less than the duration of action of fentanyl in Fentanyl Citrate Injection, carefully monitor the patient until spontaneous respiration is reliably reestablished. If the response to an opioid antagonist is suboptimal or only brief in nature, administer additional antagonist as directed by the product's prescribing information.

In an individual physically dependent on opioids, administration of the recommended usual dosage of the antagonist will precipitate an acute withdrawal syndrome. The severity of the withdrawal symptoms experienced will depend on the degree of physical dependence and the dose of the antagonist administered. If a decision is made to treat serious respiratory depression in the physically dependent patient, administration of the antagonist should be initiated with care and by titration with smaller than usual doses of the antagonist.

11 DESCRIPTION

Fentanyl Citrate Injection is a Schedule II controlled drug substance and is an opioid agonist. Fentanyl Citrate Injection, USP is a sterile, clear, colorless, non-pyrogenic, preservative free aqueous solution for intravenous or intramuscular injection.

Fentanyl Citrate Injection contains fentanyl citrate as the active pharmaceutical ingredient. The chemical name is N-(1-Phenethylpiperidin-4-yl)-N-phenylpropionamide 2-hydroxy-1,2,3-propanetricarboxylate. The molecular weight is 528.60 g/mol. Its molecular formula is C22H28N2O • C6H8O7, and it has the following chemical structure:

Each mL of Fentanyl Citrate Injection contains 78.5 mcg fentanyl citrate (equivalent to 50 mcg fentanyl base), sodium hydroxide (q.s.) as pH adjuster, in water for injection. Fentanyl Citrate Injection pH is between 4.5 to 7.0.

12 CLINICAL PHARMACOLOGY

12.1 Mechanism of Action

Fentanyl Citrate Injection is an opioid agonist, whose principal actions of therapeutic value are analgesia and sedation.

12.2 Pharmacodynamics

Effects on the Central Nervous System

Fentanyl produces respiratory depression by direct action on brain stem respiratory centers. The respiratory depression involves a reduction in the responsiveness of the brain stem respiratory centers to both increases in carbon dioxide tension and electrical stimulation.

Fentanyl causes miosis, even in total darkness. Pinpoint pupils are a sign of opioid overdose but are not pathognomonic (e.g., pontine lesions of hemorrhagic or ischemic origins may produce similar findings). Marked mydriasis rather than miosis may be seen due to hypoxia in overdose situations.

Effects on the Gastrointestinal Tract and Other Smooth Muscle

Fentanyl causes a reduction in motility associated with an increase in smooth muscle tone in the antrum of the stomach and duodenum. Digestion of food in the small intestine is delayed and propulsive contractions are decreased. Propulsive peristaltic waves in the colon are decreased, while tone may be increased to the point of spasm, resulting in constipation. Other opioid-induced effects may include a reduction in biliary and pancreatic secretions, spasm of sphincter of Oddi, and transient elevations in serum amylase.

Effects on the Cardiovascular System

Fentanyl produces peripheral vasodilation which may result in orthostatic hypotension or syncope. Manifestations of histamine release and/or peripheral vasodilation may include pruritus, flushing, red eyes, sweating, and/or orthostatic hypotension.

Effects on the Endocrine System

Opioids inhibit the secretion of adrenocorticotropic hormone (ACTH), cortisol, and luteinizing hormone (LH) in humans. They also stimulate prolactin, growth hormone (GH) secretion, and pancreatic secretion of insulin and glucagon.

Chronic use of opioids may influence the hypothalamic-pituitary-gonadal axis, leading to androgen deficiency that may manifest as low libido, impotence, erectile dysfunction, amenorrhea, or infertility. The causal role of opioids in the clinical syndrome of hypogonadism is unknown because the various medical, physical, lifestyle, and psychological stressors that may influence gonadal hormone levels have not been adequately controlled for in studies conducted to date [see Adverse Reactions (6)].

Effects on the Immune System

Opioids have been shown to have a variety of effects on components of the immune system in in vitro and animal models. The clinical significance of these findings is unknown. Overall, the effects of opioids appear to be modestly immunosuppressive.

Concentration–Efficacy Relationships

A dose of 100 mcg (0.1 mg) (2.0 mL) of Fentanyl Citrate Injection is approximately equivalent in analgesic activity to 10 mg of morphine or 75 mg of meperidine.

The minimum effective analgesic concentration will vary widely among patients, especially among patients who have been previously treated with potent agonist opioids. The minimum effective analgesic concentration of fentanyl for any individual patient may increase over time due to an increase in pain, the development of a new pain syndrome and/or the development of analgesic tolerance [see Dosage and Administration (2.1)].

The onset of action of fentanyl is almost immediate when the drug is given intravenously; however, the maximal analgesic effect may not be noted for several minutes. The usual duration of action of the analgesic effect is 30 to 60 minutes after a single intravenous dose of up to 100 mcg (0.1 mg) (2 mL). Following intramuscular administration, the onset of action is from seven to eight minutes and the duration of action is one to two hours.

Concentration–Adverse Reaction Relationships

There is a relationship between increasing fentanyl plasma concentration and increasing frequency of dose-related opioid adverse reactions such as nausea, vomiting, CNS effects, and respiratory depression. In opioid-tolerant patients, the situation may be altered by the development of tolerance to opioid-related adverse reactions [see Dosage and Administration (2.1, 2.2)].

The onset of action of fentanyl is almost immediate when the drug is given intravenously; however, the maximal respiratory depressant effect may not be noted for several minutes. As with longer acting opioid analgesics, the duration of the respiratory depressant effect of fentanyl may be longer than the analgesic effect. The following observations have been reported concerning altered respiratory response to CO2 stimulation following administration of fentanyl citrate:

- Diminished sensitivity to CO2 stimulation may persist longer than depression of respiratory rate. (Altered sensitivity to CO2 stimulation has been demonstrated for up to four hours following a single dose of 600 mcg (0.6 mg) (12 mL) fentanyl citrate to healthy volunteers). Fentanyl frequently slows the respiratory rate, duration and degree of respiratory depression being dose-related.
- The peak respiratory depressant effect of a single intravenous dose of Fentanyl Citrate Injection is noted 5 to 15 minutes following injection [see Warnings and Precautions (5.2)].

12.3 Pharmacokinetics

Fentanyl Citrate Injection is administered by the intravenous or intramuscular route. The pharmacokinetics of fentanyl can be described as a three-compartment model.

Distribution

Fentanyl plasma protein binding capacity decreases with increasing ionization of the drug. Alterations in pH may affect its distribution between plasma and the central nervous system. It accumulates in skeletal muscle and fat, and is released slowly into the blood. The volume of distribution for fentanyl is 4 L/kg. It has a distribution time of 1.7 minutes and redistribution time of 13 minutes.

Elimination

The terminal elimination half-life is 219 minutes.

Fentanyl, which is primarily transformed in the liver, demonstrates a high first pass clearance and releases approximately 75% of an intravenous dose in urine, mostly as metabolites with less than 10% representing the unchanged drug. Approximately 9% of the dose is recovered in the feces, primarily as metabolites.

13 NONCLINICAL TOXICOLOGY

13.1 Carcinogenesis, Mutagenesis, Impairment of Fertility

Carcinogenesis

Long-term studies in animals to evaluate the carcinogenic potential of fentanyl citrate injection have not been conducted.

Mutagenesis

Studies in animals to evaluate the mutagenic potential of fentanyl have not been conducted.

Impairment of Fertility

Decreased pregnancy rates occurred in a multigenerational study in which pregnant rats were treated subcutaneously during the first 21 days of pregnancy with 160 mcg/kg to 1250 mcg/kg fentanyl (0.26 times to 2.0 times a human dose of 100 mcg/kg based on body surface area).

Studies in animals to characterize the effect of fentanyl on male fertility have not been conducted.

16 HOW SUPPLIED/STORAGE AND HANDLING

Fentanyl Citrate Injection, USP equivalent to 50 mcg fentanyl base per mL are available in single-dose glass containers as follows:

NDC 17478-030-02 | 100 mcg/2 mL (50 mcg/mL) single-dose ampules in packages of 10
NDC 17478-030-05 | 250 mcg/5 mL (50 mcg/mL) single-dose ampules in packages of 10
NDC 17478-030-10 | 500 mcg/10 mL (50 mcg/mL) single-dose ampules in packages of 5
NDC 17478-030-20 | 1,000 mcg/20 mL (50 mcg/mL) single-dose ampules in packages of 5
NDC 17478-030-25 | 100 mcg/2 mL (50 mcg/mL) single-dose ampules in packages of 25
NDC 17478-030-55 | 250 mcg/5 mL (50 mcg/mL) single-dose ampules in packages of 25
NDC 17478-031-50 | 2,500 mcg/50 mL (50 mcg/mL) single-dose vial in single pack

Storage: Store at room temperature 20°C to 25°C (68°F to 77°F); excursions permitted between 15°C and 30°C (59°F and 86°F). Protect from light.

AKORN

Manufactured by: Akorn
Lake Forest, IL 60045

AFCA0N Rev. 03/22

Principal Display Panel Text for Container Label:

NDC 17478-030-02 2 mL Ampule

Fentanyl Citrate

Injection, USP CII

100 mcg/2 mL (50 mcg/mL)*

FOR INTRAVENOUS OR
INTRAMUSCULAR USE Rx only

Principal Display Panel Text for Carton Label:

NDC 17478-030-02 10 Ampules (2 mL each)

Fentanyl Citrate

Injection, USP CII

100 mcg/2 mL

(50 mcg/mL)*

Single-dose Ampule FOR INTRAVENOUS OR INTRAMUSCULAR USE

Discard unused portion.

Rx only Akorn Logo